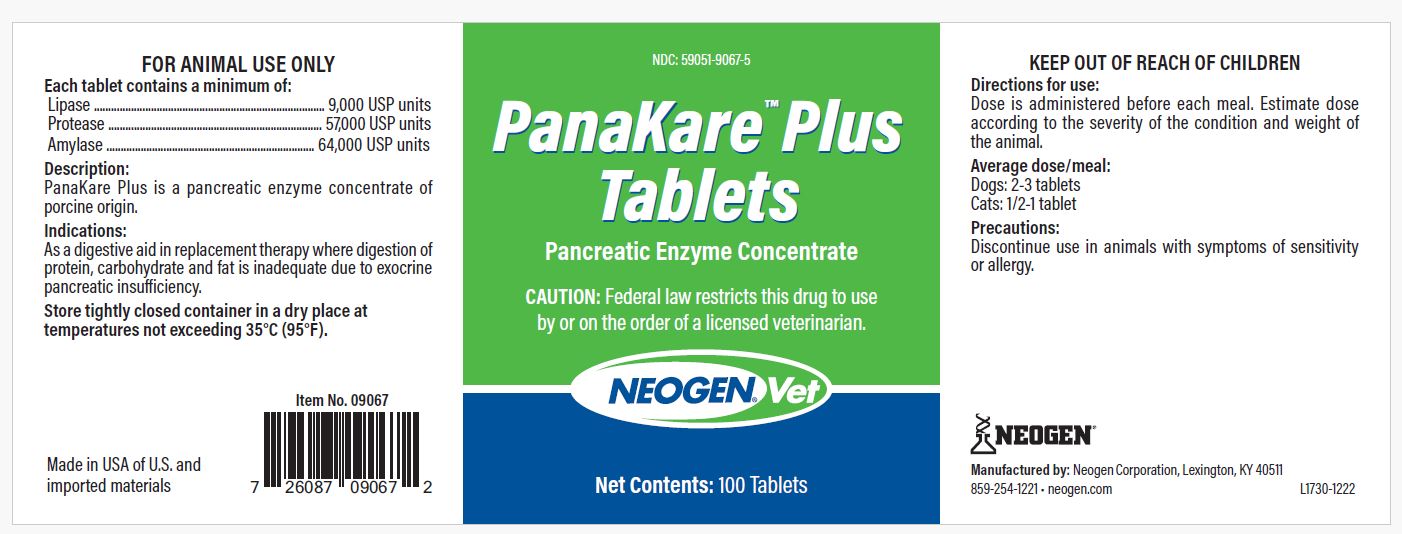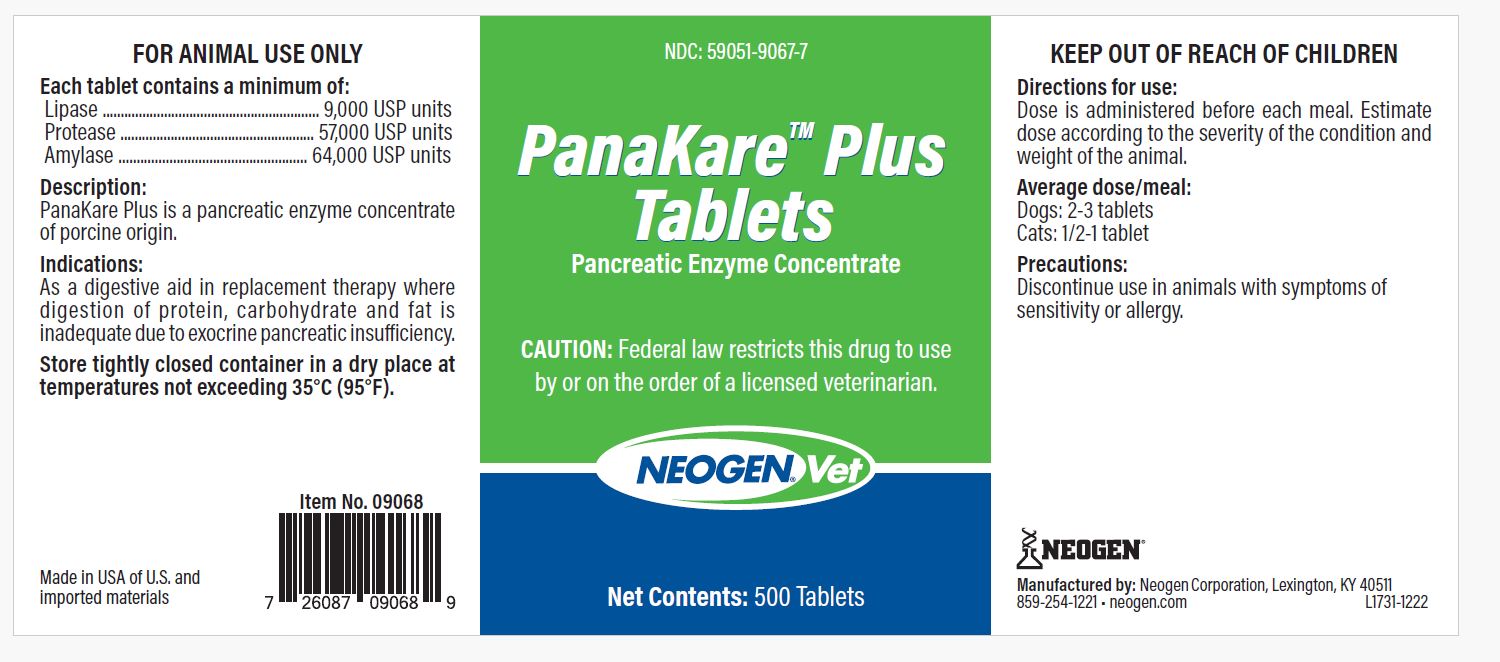 DRUG LABEL: PanaKare Plus
NDC: 59051-9067 | Form: TABLET
Manufacturer: Neogen Corporation-Mercer
Category: animal | Type: PRESCRIPTION ANIMAL DRUG LABEL
Date: 20240123

ACTIVE INGREDIENTS: PANCRELIPASE LIPASE 9000 [iU]/1 1; PANCRELIPASE AMYLASE 64000 [iU]/1 1; PANCRELIPASE PROTEASE 57000 [iU]/1 1

DESCRIPTION

PanaKare Plus Tablets

Pancreatic Enzyme Concentrate

CAUTION: Federal law restricts this drug to use by or on the order of a licensed veterinarian.

FOR ANIMAL USE ONLY

COMPONENTS

Each tablet contains a minimum of:

Lipase..............................9,000 USP units

Protease.........................57,000 USP units

Amylase..........................64,000 USP units

Description:

PanaKare Plus is a pancreatic enzyme concentrate of porcine origin.

Precautions:

Discontinue use in animals with symptoms of sensitivity or allergy.

Made in the USA of U.S. and imported materials

KEEP OUT OF REACH OF CHILDREN

Indications:

As a digestive aid in replacement therapy where digestion of protein, carbohydrate and fat is inadequate due to exocrine pancreatic insufficiency.

Directions for use:

Dose is administered before each meal. Estimate dose according to the severity of the condition and weight of the animal.

Average dose/meal:

Dogs: 2-3 tablets

Cats: 1/2-1 tablet

STORAGE AND HANDLING

Store tightly closed container in a dry place at temperatures not exceeding 35°C (95°F).

Manufactured by: Neogen Corporation

Lexington, KY 40511 859-254-1221

neogen.com

PRINCIPAL DISPLAY PANEL - 500 Tablet Bottle

NDC: 59051-9067-7

PanaKare Plus Tablets

Pancreatic Enzyme Concentrate

CAUTION: Federal law restricts this drug to use by or on the order of a licensed veterinarian.

Net Contents: 500 Tablets

PRINCIPAL DISPLAY PANEL - 100 Tablet Bottle

NDC: 59051-9067-5

PanaKare Plus Tablets

Pancreatic Enzyme Concentrate

CAUTION: Federal law restricts this drug to use by or on the order of a licensed veterinarian.

Net Contents: 100 Tablets